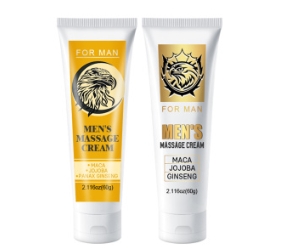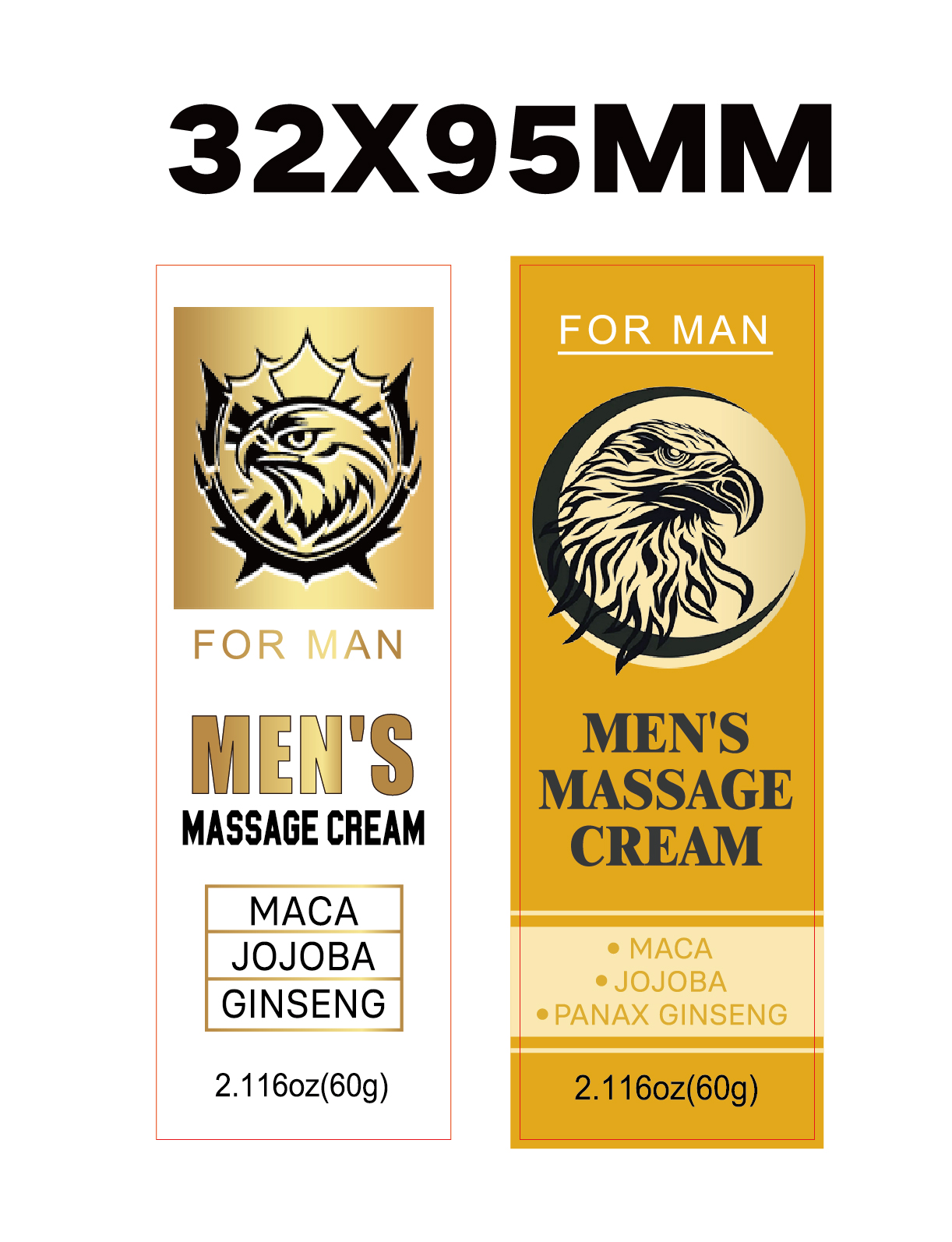 DRUG LABEL: Mens Massage Cream
NDC: 84025-285 | Form: CREAM
Manufacturer: Guangzhou Yanxi Biotechnology Co., Ltd
Category: otc | Type: HUMAN OTC DRUG LABEL
Date: 20241219

ACTIVE INGREDIENTS: GLYCERIN 3 mg/60 g; PANTHENOL 2 mg/60 g
INACTIVE INGREDIENTS: WATER

DOSAGE AND ADMINISTRATION

Clean The Private Parts, Squeeze Out The Right Amount Of Cream And Smear The Required Parts

WARNINGS

Keep out of children

INACTIVE INGREDIENT

Aqua

INDICATIONS AND USAGE

For daily skin care

Keep out of children

PURPOSE

Men's energy strength massage spary god of war seven times a night